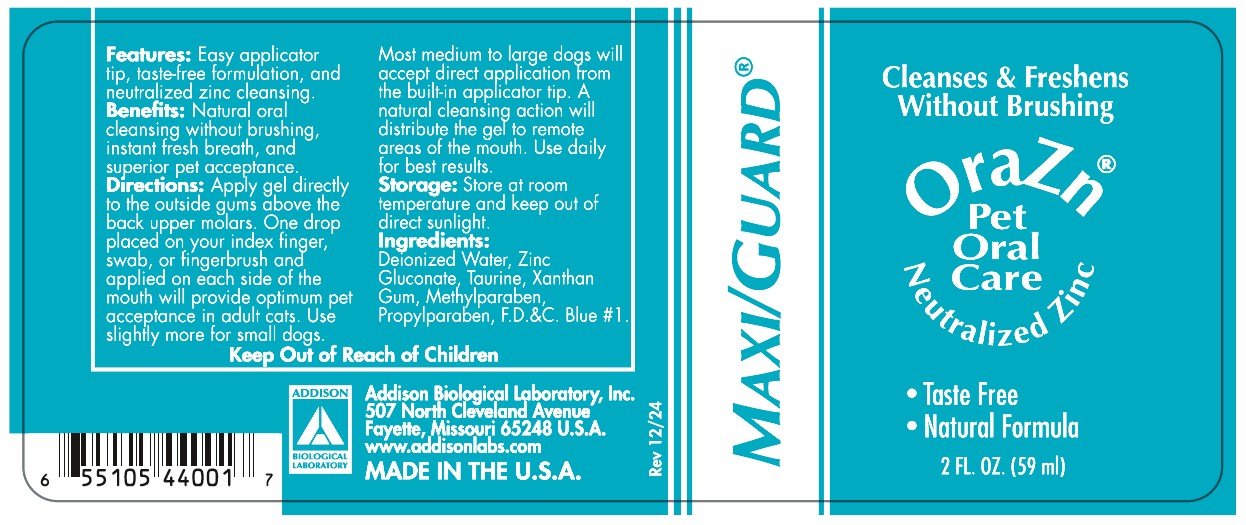 DRUG LABEL: OraZn
NDC: 86045-9200 | Form: GEL
Manufacturer: Addison Biological Laboratory, Inc.
Category: animal | Type: OTC ANIMAL DRUG LABEL
Date: 20251201

ACTIVE INGREDIENTS: ZINC GLUCONATE 0.022 g/1 mL
INACTIVE INGREDIENTS: WATER; TAURINE; METHYLPARABEN; PROPYLPARABEN; FD&C BLUE NO. 1; XANTHAN GUM

OraZn

INFORMATION FOR OWNERS/CAREGIVERS

Features: Easy applicator tip, taste free formulation, and neutralized zinc cleansing.

Benefits: Natural oral cleansing without brushing, instant fresh breath, and superior pet acceptance.

INSTRUCTIONS FOR USE

Directions: Apply gel directly to the outside gums above the back upper molars. One drop placed on your index finger, swab, or fingerbrush and applied on each side of the mouth will provide optimum pet acceptance in adult cats. Use slightly more for small dogs. Most medium to large dogs will accept direct application from the built-in applicator tip. A natural cleansing action will distribute the gel to remote areas of the mouth. Use daily for best results.

STORAGE AND HANDLING

Storage: Store at room temperature and keep out of direct sunlight.

ACTIVE INGREDIENT

Ingredients: Deionized Water, Zinc Gluconate, Taurine, Xanthan Gum, Methylparaben, Propylparaben, F.D.&C. Blue #1.

Keep out of reach of children.

Addison Biological Laboratory, Inc.

507 North Cleveland Avenue

Fayette, Missouri 65248 U.S.A.

www.addisonlabs.com

MADE IN THE U.S.A.

Rev. 12/24

Principle Display Panel - OraZn

Cleanses & Freshens
Without Brushing
OraZn®
Pet
Oral
Care

Neutralized Zinc

- Taste Free
- Natural Formula

2 FL. OZ (59ml)

MAXI/GUARD®

Features: Easy applicator tip, taste free formulation, and neutralized zinc cleansing.
Benefits: Natural oral cleansing without brushing, instant fresh breath, and superior pet acceptance.
Directions: Apply gel directly to the outside gums above the back upper molars. One drop placed on your index finger, swab, or fingerbrush and applied on each side of the mouth will provide optimum pet acceptance in adult cats. Use slightly more for small dogs. Most medium to large dogs will accept direct application from the built-in applicator tip. A natural cleansing action will distribute the gel to remote areas of the mouth. Use daily for best results.
Storage: Store at room temperature and keep out of direct sunlight.

Ingredients: Deionized Water, Zinc Gluconate, Taurine, Xanthan Gum, Methylparaben, Propylparaben, F.D.&C. Blue #1.

Keep out of reach of children.

Addison Biological Laboratory, Inc.
507 North Cleveland Avenue
Fayette, Missouri 65248 U.S.A.
www.addisonlabs.com
MADE IN THE U.S.A.
Rev. 12/24